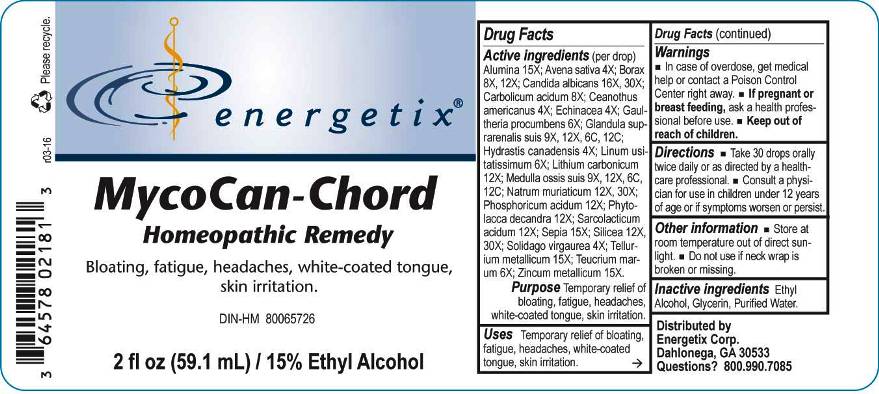 DRUG LABEL: MycoCan-Chord
NDC: 64578-0071 | Form: LIQUID
Manufacturer: Energetix Corp
Category: homeopathic | Type: HUMAN OTC DRUG LABEL
Date: 20160330

ACTIVE INGREDIENTS: ALUMINUM OXIDE 15 [hp_X]/1 mL; AVENA SATIVA FLOWERING TOP 4 [hp_X]/1 mL; SODIUM BORATE 8 [hp_X]/1 mL; CANDIDA ALBICANS 16 [hp_X]/1 mL; PHENOL 8 [hp_X]/1 mL; CEANOTHUS AMERICANUS LEAF 4 [hp_X]/1 mL; ECHINACEA ANGUSTIFOLIA 4 [hp_X]/1 mL; GAULTHERIA PROCUMBENS TOP 6 [hp_X]/1 mL; SUS SCROFA ADRENAL GLAND 9 [hp_X]/1 mL; GOLDENSEAL 4 [hp_X]/1 mL; FLAX SEED 6 [hp_X]/1 mL; LITHIUM CARBONATE 12 [hp_X]/1 mL; SUS SCROFA BONE MARROW 9 [hp_X]/1 mL; SODIUM CHLORIDE 12 [hp_X]/1 mL; PHOSPHORIC ACID 12 [hp_X]/1 mL; PHYTOLACCA AMERICANA ROOT 12 [hp_X]/1 mL; LACTIC ACID, L- 12 [hp_X]/1 mL; SEPIA OFFICINALIS JUICE 15 [hp_X]/1 mL; SILICON DIOXIDE 12 [hp_X]/1 mL; SOLIDAGO VIRGAUREA FLOWERING TOP 4 [hp_X]/1 mL; TELLURIUM 15 [hp_X]/1 mL; TEUCRIUM MARUM 6 [hp_X]/1 mL; ZINC 15 [hp_X]/1 mL
INACTIVE INGREDIENTS: WATER; GLYCERIN; ALCOHOL

Drug Facts:

ACTIVE INGREDIENTS:

Alumina 15X; Avena sativa 4X; Borax 8X, 12X; Candida albicans 16X, 30X; Carbolicum acidum 8X; Ceanothus americanus 4X; Echinacea 4X; Gaultheria procumbens 6X; Glandula suprarenalis suis 9X, 12X, 6C, 12C; Hydrastis canadensis 4X; Linum usitatissimum 6X; Lithium carbonicum 12X; Medulla ossis suis 9X, 12X, 6C, 12C; Natrum muriaticum 12X, 30X; Phosphoricum acidum 12X; Phytolacca decandra 12X; Sarcolacticum acidum 12X; Sepia 15X; Silicea 12X, 30X; Solidago virgaurea 4X; Tellurium metallicum 15X; Teucrium marum 6X; Zincum metallicum 15X.

PURPOSE:

Temporary relief of bloating, fatigue, headaches, white-coated tongue, skin irritation.

WARNINGS:

In case of overdose, get medical help or contact a Poison Control Center right away.
If pregnant or breast feeding, ask a health professional before use.
Keep out of reach of children.

Other information
Store in a cool, dry place out of direct sunlight.
Do not use if neck wrap is broken or missing.

Keep out of reach of children. In case of overdose, get medical help or contact a Poison Control Center right away.

DIRECTIONS:

Take 30 drops orally twice daily or as directed by a healthcare professional.
Consult a physician for use in children under 12 years of age or if symptoms worsen or persist.

USES:

Temporary relief of bloating, fatigue, headaches, white-coated tongue, skin irritation.

INACTIVE INGREDIENTS:

Ethyl Alcohol, Glycerin, Purified Water

QUESTIONS:

Distributed by
Energetix Corp.
Dahlonega, GA 30533
Questions: 800.990.7085

PACKAGE LABEL DISPLAY:

energetix

MycoCan-Chord

Homeopathic Remedy

Bloating, fatigue, headaches, white-coated tongue, skin irritation.

2 fl oz (59.1 mL)